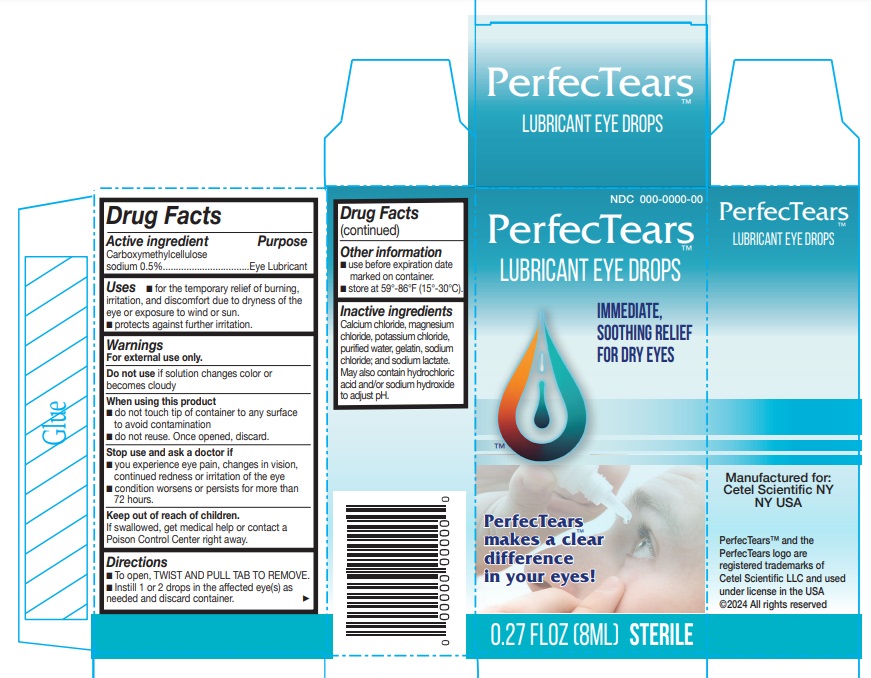 DRUG LABEL: PerfecTears
NDC: 84535-001 | Form: LIQUID
Manufacturer: Cetel Scientific LLC
Category: otc | Type: HUMAN OTC DRUG LABEL
Date: 20240723

ACTIVE INGREDIENTS: CARBOXYMETHYLCELLULOSE SODIUM 5 mg/1 mL; CARBOXYMETHYLCELLULOSE 5 mg/1 mL
INACTIVE INGREDIENTS: CALCIUM CHLORIDE; MAGNESIUM CHLORIDE; POTASSIUM CHLORIDE; WATER; SODIUM CHLORIDE; SODIUM LACTATE; HYDROCHLORIC ACID; SODIUM HYDROXIDE; GELATIN

Active ingredient

Carboxymethylcellulose sodium 0.5%

Purpose

Eye Lubricant

Uses

- For temporary relief of burning, irritation and discomfort due to dryness of the eye or exposure to wind or sun
- protectant against further irritation

Warnings

For external use only.

Do not useif solution changes color or becomes cloudy

When using this product

- do not touch tip of container to any surface to avoid contamination
- do not reuse. Once opened, discard.

Stop use and ask a doctor if

- you experience eye pain, changes in vision,continued redness or irritation of the eye
- condition worsens or persists for more than 72 hours.

Keep out of reach of children.
If swallowed, get medical help or contact a Poison Control Center right away.

Directions

- To open, TWIST AND PULL TAB TO REMOVE.
- Instill 1 or 2 drops in the affected eye(s) as needed and discard container.

Other information

- use before expiration date marked on container.
- store at 59°-86°F (15°-30°C).

Inactive ingredients

Calcium chloride, magnesium chloride, potassium chloride, purified water, gelatin, sodium chloride; and sodium lactate.May also contain hydrochloric acid and/or sodium hydroxide to adjust pH.